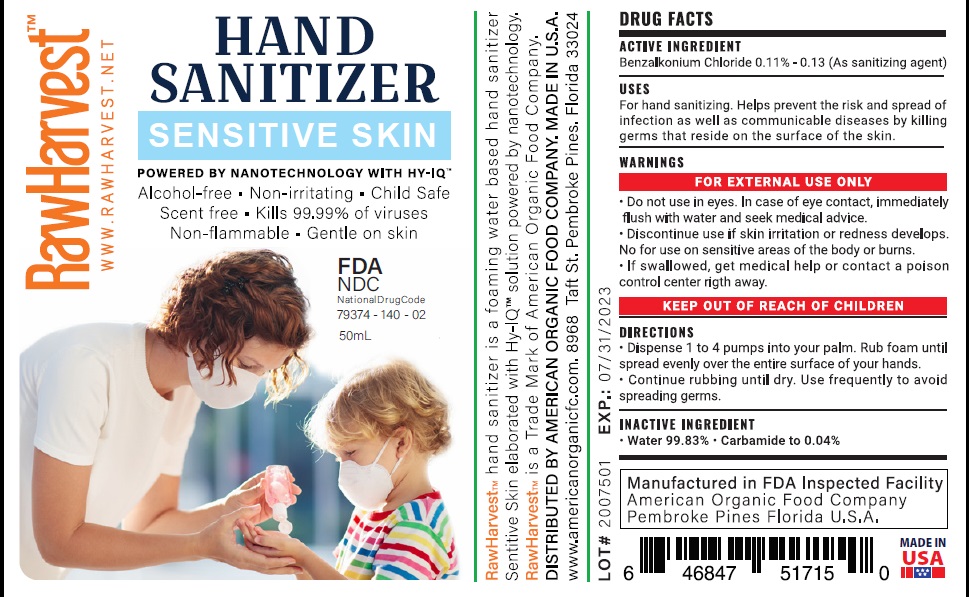 DRUG LABEL: RawHarvest Hand Sanitizer Sensitive Skin
NDC: 79374-140 | Form: LIQUID
Manufacturer: AMERICAN ORGANIC FOOD COMPANY LLC
Category: otc | Type: HUMAN OTC DRUG LABEL
Date: 20200702

ACTIVE INGREDIENTS: BENZALKONIUM CHLORIDE 0.13 g/100 mL
INACTIVE INGREDIENTS: UREA; WATER

Active Ingredient

Benzalkonium Chloride 0.11% - 0.13%

Purpose

Antiseptic

Use

For hand sanitizing. Helps prevent the risk and spread of infection as well as communicable diseases by killing germs that reside on the surface of the skin.

Warnings

Do not use in eyes. In case of eye contact, immediately flush with water and seek medical advice.
Discontinue use if skin irritation or redness develops.
No for use on sensitive areas of the body or burns.

KEEP OUT OF REACH OF CHILDREN

If swallowed, get medical help or contact a Poison Control Center right away.

Directions

Dispense 1 to 4 pumps into your palm. Rub foam until spread evenly over the entire surface of your hands.
Continue rubbing until dry. Use frequently to avoid spreading germs.

Inactive ingredients

Water 99.83%, Carbamide to 0.04%